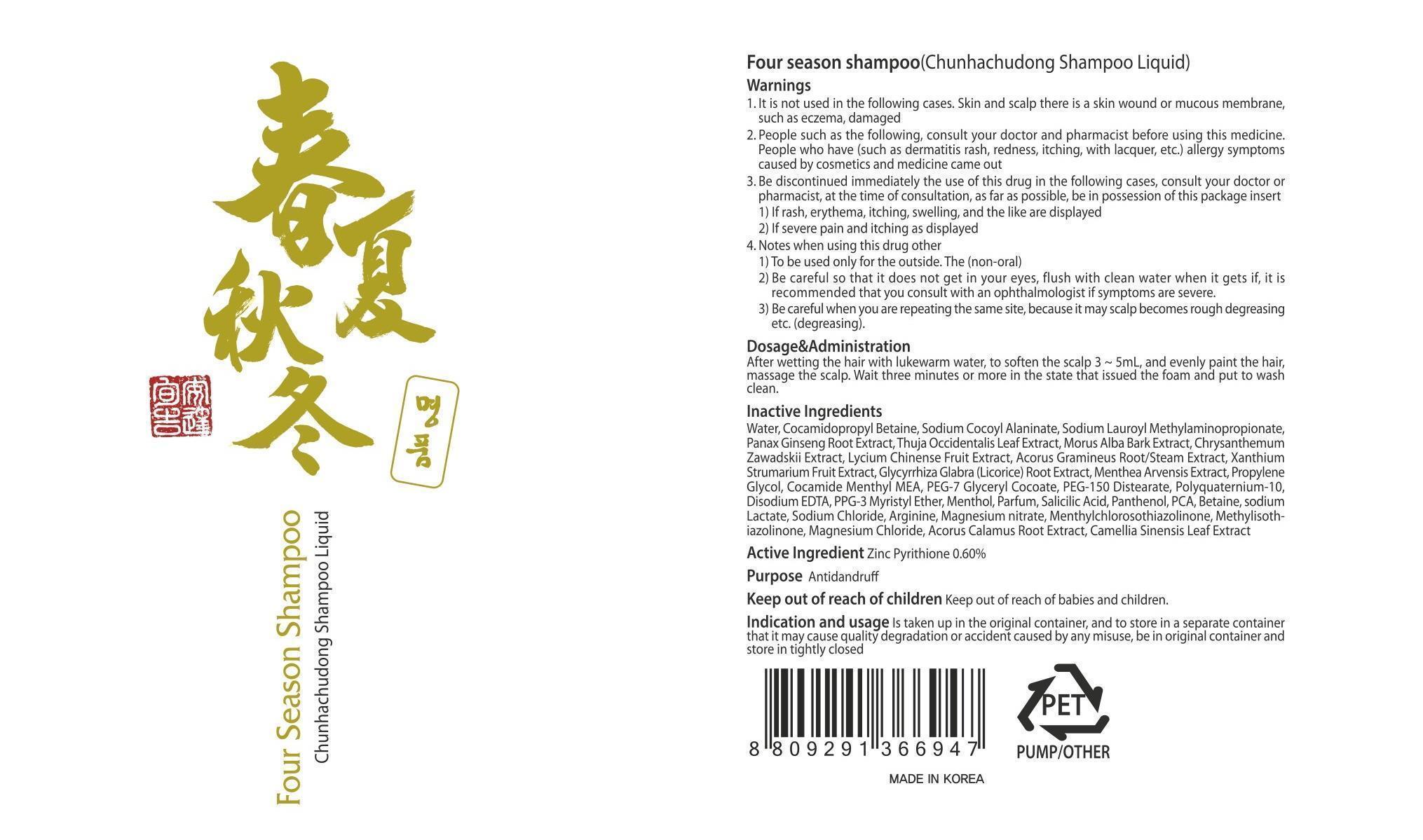 DRUG LABEL: Four Season
NDC: 61616-010 | Form: SHAMPOO
Manufacturer: OneLineSun Co., Ltd.
Category: otc | Type: HUMAN OTC DRUG LABEL
Date: 20140127

ACTIVE INGREDIENTS: PYRITHIONE ZINC 1.8 mg/300 mL
INACTIVE INGREDIENTS: Water; Cocamidopropyl Betaine

ACTIVE INGREDIENT

Active Ingredient: Zinc Pyrithione 0.60%

INACTIVE INGREDIENT

Inactive Ingredients:
Water, Cocamidopropyl Betaine, Sodium Cocoyl Alaninate, Sodium Lauroyl Methylaminopropionate, Panax Ginseng Root Extract, Thuja Occidentalis Leaf Extract, Morus Alba Bark Extract, Chrysanthemum Zawadskii Extract, Lycium Chinense Fruit Extract, Acorus Gramineus Root/Steam Extract, Xanthium Strumarium Fruit Extract, Glycyrrhiza Glabra (Licorice) Root Extract, Menthea Arvensis Extract, Propylene Glycol, Cocamide Menthyl MEA, PEG-7 Glyceryl Cocoate, PEG-150 Distearate, Polyquaternium-10, Disodium EDTA, PPG-3 Myristyl Ether, Menthol, Parfum, Salicilic Acid, Panthenol, PCA, Betaine, sodium Lactate, Sodium Chloride, Arginine, Magnesium nitrate, Menthylchlorosothiazolinone, Methylisothiazolinone, Magnesium Chloride, Acorus Calamus Root Extract, Camellia Sinensis Leaf Extract

PURPOSE

Purpose: Antidandruff

WARNINGS

1. It is not used in the following cases.
Skin and scalp there is a skin wound or mucous membrane, such as eczema, damaged
2. People such as the following, consult your doctor and pharmacist before using this medicine
People who have (such as dermatitis rash, redness, itching, with lacquer, etc.) allergy symptoms caused by cosmetics and medicine came out
3. Be discontinued immediately the use of this drug in the following cases, consult your doctor or pharmacist, at the time of consultation, as far as possible, be in possession of this package insert
1) If rash, erythema, itching, swelling, and the like are displayed
2) If severe pain and itching as displayed
4. Notes when using this drug other
1) To be used only for the outside. The (non-oral)
2) Be careful so that it does not get in your eyes, flush with clean water when it gets if, it is recommended that you consult with an ophthalmologist if symptoms are severe.
3) Be careful when you are repeating the same site, because it may scalp becomes rough degreasing etc. (degreasing).

KEEP OUT OF REACH OF CHILDREN: Keep out of reach of babies and children.

INDICATIONS AND USAGE

Is taken up in the original container, and to store in a separate container that it may cause quality degradation or accident caused by any misuse, be in original container and store in tightly closed.

DOSAGE AND ADMINISTRATION

After wetting the hair with lukewarm water, to soften the scalp 3-5mL, and evenly paint the hair, massage the scalp.
Wait three minutes or more in the state that issued the foam and put to wash clean.